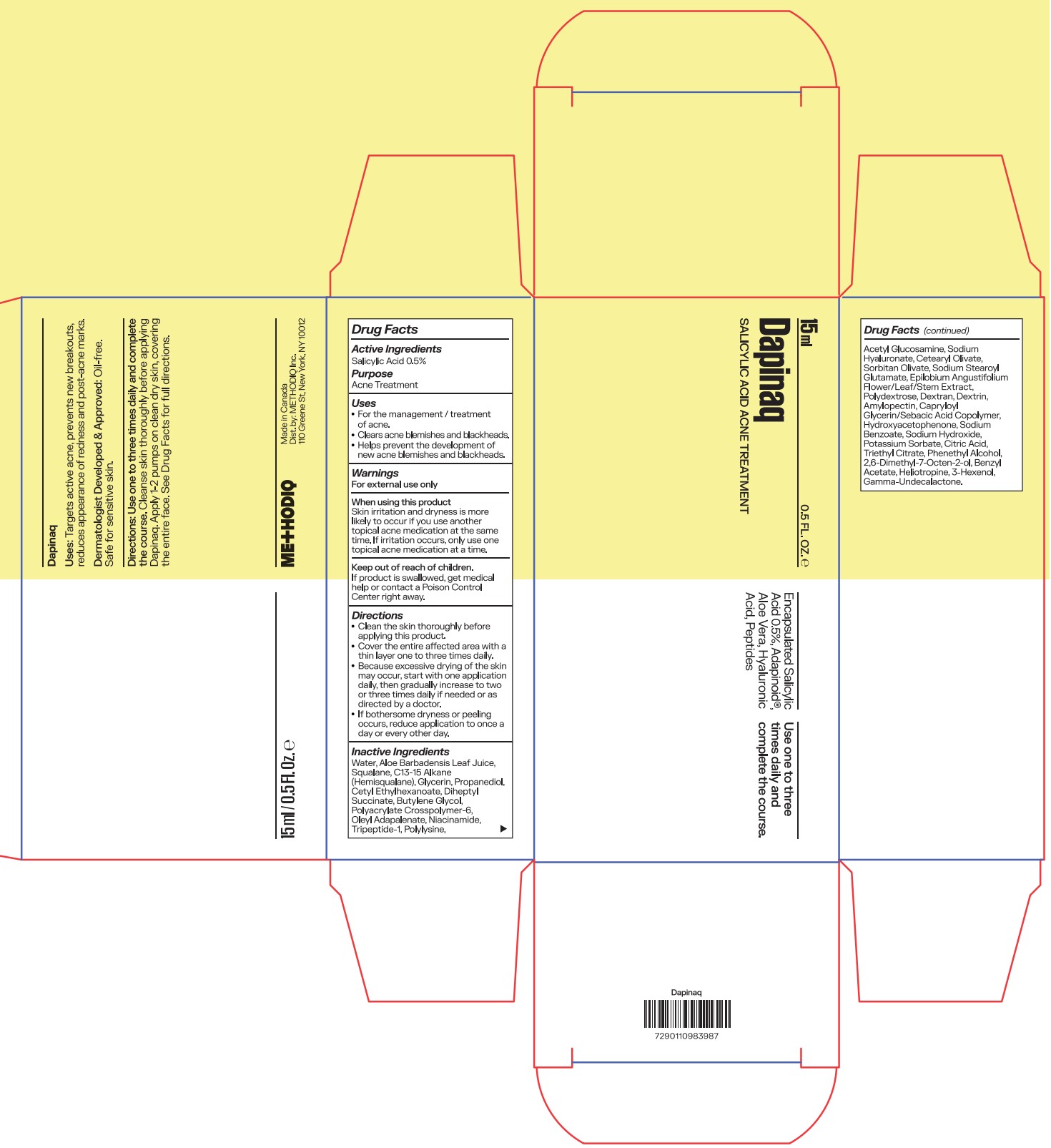 DRUG LABEL: Dapinaq
NDC: 87110-002 | Form: CREAM
Manufacturer: METHODIQ INC.
Category: otc | Type: HUMAN OTC DRUG LABEL
Date: 20251110

ACTIVE INGREDIENTS: SALICYLIC ACID 5 mg/1 mL
INACTIVE INGREDIENTS: ACETYL GLUCOSAMINE; WATER; PROPANEDIOL; POLYACRYLATE CROSSPOLYMER-6; BUTYLENE GLYCOL; SORBITAN OLIVATE; GLYCERIN; NIACINAMIDE; BENZYL ACETATE; ALOE BARBADENSIS LEAF JUICE; SQUALANE; OLEYL ADAPALENATE; TRIPEPTIDE-1; SODIUM STEAROYL GLUTAMATE; EPILOBIUM ANGUSTIFOLIUM FLOWERING TOP; POLYDEXTROSE; CAPRYLOYL GLYCERIN/SEBACIC ACID COPOLYMER (2000 MPA.S); SODIUM BENZOATE; POTASSIUM SORBATE; CITRIC ACID; TRIETHYL CITRATE; PHENETHYL ALCOHOL; 2,6-DIMETHYL-7-OCTEN-2-OL; HELIOTROPINE; AMYLOPECTIN, UNSPECIFIED SOURCE; CETEARYL OLIVATE; DEXTRAN 1; SODIUM HYDROXIDE; C13-15 ALKANE; SODIUM HYALURONATE; HYDROXYACETOPHENONE; GAMMA-UNDECALACTONE; CETYL ETHYLHEXANOATE; DIHEPTYL SUCCINATE; POLY-L-LYSINE (30000-70000 MW); DEXTRIN, CORN; 3-HEXENOL

Dapinaq

Active ingredients

Salicylic Acid 0.5%

Purpose

Salicylic Acid 0.5%.......................Acne Treatment

Uses

- For the management / treatment of acne.
- Clears acne blemishes and blackheads.
- Helps prevent the development of new acne blemishes and blackheads.

Warnings

For external use only

When using this product
Skin irritation and dryness is more likely to occur if you use another topical acne medication at the same time. If irritation occurs, only use one topical acne medication at a time.

Keep out of reach of children.
If product is swallowed, get medical help or contact a Poison Control Center right away.

Directions

- Clean the skin thoroughly before applying this product.
- Cover the entire affected area with a thin layer one to three times daily.
- Because excessive drying of the skin may occur, start with one application daily, then gradually increase to two or three times daily if needed or as directed by a doctor.
- If bothersome dryness or peeling occurs, reduce application to once a day or every other day.

Inactive ingredients

Water, Aloe Barbadensis Leaf Juice, Squalane, C13-15 Alkane (Hemisqualane), Glycerin, Propanediol, Cetyl Ethylhexanoate, Diheptyl Succinate, Butylene Glycol, Polyacrylate Crosspolymer-6, Oleyl Adapalenate, Niacinamide, Tripeptide-1, Polylysine, Acetyl Glucosamine, Sodium Hyaluronate, Cetearyl Olivate, Sorbitan Olivate, Sodium Stearoyl Glutamate, Epilobium Angustifolium Flower/Leaf/Stem Extract, Polydextrose, Dextran, Dextrin, Amylopectin, Capryloyl Glycerin/Sebacic Acid Copolymer, Hydroxyacetophenone, Sodium Benzoate, Sodium Hydroxide, Potassium Sorbate, Citric Acid, Triethyl Citrate, Phenethyl Alcohol, 2,6-Dimethyl-7-Octen-2-ol, Benzyl Acetate, Heliotropine, 3-Hexenol, Gamma-Undecalactone

PACKAGE LABEL

15ml

0.5 Fl. Oz.

Dapinaq

Salicylic Acid Acne Treatment